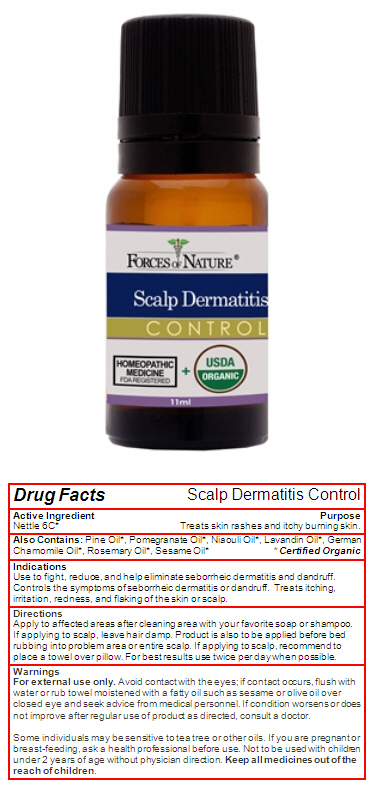 DRUG LABEL: Scalp Dermatitis
NDC: 51393-4008 | Form: SOLUTION/ DROPS
Manufacturer: Forces of Nature
Category: homeopathic | Type: HUMAN OTC DRUG LABEL
Date: 20131001

ACTIVE INGREDIENTS: URTICA DIOICA 6 [hp_C]/1000 mL
INACTIVE INGREDIENTS: Pine Needle Oil (Pinus Sylvestris); Pomegranate Seed Oil; MELALEUCA QUINQUENERVIA LEAF OIL; Lavender Oil; Chamomile Flower Oil; Rosemary Oil; Sesame Oil

Scalp Dermatitis

Drug Facts

Active Ingredient

Nettle 6C [Certified Organic]

Purpose

Treats skin rashes and itchy burning skin.

Also Contains

Pine Oil, Pomegranate Oil, Niaouli Oil, Lavandin Oil, German Chamomile Oil, Rosemary Oil, Sesame Oil

Indications

Use to fight, reduce, and help eliminate seborrheic dermatitis and dandruff. Controls the symptoms of seborrheic dermatitis or dandruff. Treats itching, irritation, redness, and flaking of the skin or scalp.

Directions

Apply to affected areas after cleaning area with your favorite soap or shampoo.
If applying to scalp, leave hair damp. Product is also to be applied before bed rubbing into problem area or entire scalp. If applying to scalp, recommend to place a towel over pillow. For best results use twice per day when possible.

Warnings

For external use only. Avoid contact with the eyes; if contact occurs, flush with water or rub towel moistened with a fatty oil such as sesame or olive oil over closed eye and seek advice from medical personnel.

ASK DOCTOR

If condition worsens or does not improve after regular use of product as directed, consult a doctor.

Some individuals may be sensitive to tea tree or other oils.

PREGNANCY OR BREAST FEEDING

If you are pregnant or breast-feeding, ask a health professional before use.

DO NOT USE

Not to be used with children under 2 years of age without physician direction.

KEEP OUT OF REACH OF CHILDREN

Keep all medicines out of the reach of children.

PRINCIPAL DISPLAY PANEL - 11ml Bottle

FORCES OF NATURE®

Scalp Dermatitis
CONTROL

HOMEOPATHIC
MEDICINE
FDA REGISTERED
+
USDA
ORGANIC

11ml